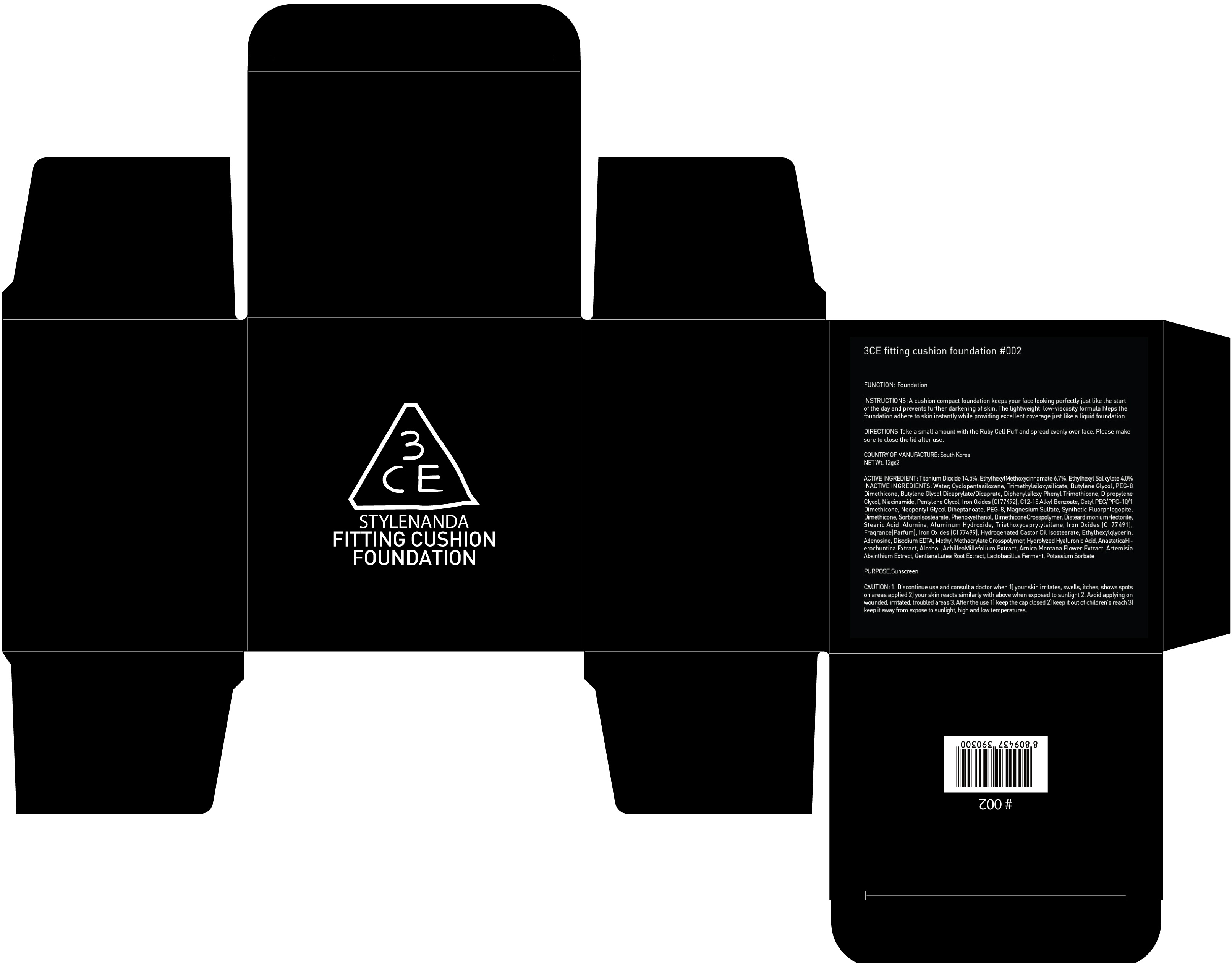 DRUG LABEL: 3CE Fitting Cushion Foundation 002
NDC: 60764-132 | Form: POWDER
Manufacturer: Nanda Co., Ltd
Category: otc | Type: HUMAN OTC DRUG LABEL
Date: 20161017

ACTIVE INGREDIENTS: Titanium Dioxide 1.74 g/12 g; Octinoxate 0.80 g/12 g; Octisalate 0.48 g/12 g
INACTIVE INGREDIENTS: Water; Butylene Glycol

ACTIVE INGREDIENT

Active Ingredient: Titanium Dioxide 14.5%, Ethylhexyl Methoxycinnamate 6.7%, Ethylhexyl Salicylate 4.0%

INACTIVE INGREDIENT

Inactive Ingredients: Water, Cyclopentasiloxane, Trimethylsiloxysilicate, Butylene Glycol, PEG-8 Dimethicone, Butylene Glycol Dicaprylate/Dicaprate, Diphenylsiloxy Phenyl Trimethicone, Dipropylene Glycol, Niacinamide, Pentylene Glycol, Iron Oxides (CI 77492), C12-15 Alkyl Benzoate, Cetyl PEG/PPG-10/1 Dimethicone, Neopentyl Glycol Diheptanoate, PEG-8, Magnesium Sulfate, Synthetic Fluorphlogopite, Dimethicone, SorbitanIsostearate, Phenoxyethanol, DimethiconeCrosspolymer, DisteardimoniumHectorite, Stearic Acid, Alumina, Aluminum Hydroxide, Triethoxycaprylylsilane, Iron Oxides (CI 77491), Fragrance(Parfum), Iron Oxides (CI 77499), Hydrogenated Castor Oil Isostearate, Ethylhexylglycerin, Adenosine, Disodium EDTA, Methyl Methacrylate Crosspolymer, Hydrolyzed Hyaluronic Acid, AnastaticaHierochuntica Extract, Alcohol, AchilleaMillefolium Extract, Arnica Montana Flower Extract, Artemisia Absinthium Extract, GentianaLutea Root Extract, Lactobacillus Ferment, Potassium Sorbate

PURPOSE

Purpose: Sunscreen

CAUTION

CAUTION: 1. Discontinue use and consult a doctor when - your skin irritates, swells, itches, shows spots on areas applied - your skin reacts similarly with above when exposed to sunlight 2. Avoid applying on wounded, irritated, troubled areas 3. After the use - keep the cap closed - keep it out of children's reach - keep it away from expose to sunlight, high and low temperatures

DESCRIPTION

INSTRUCTIONS: A Cushion compact foundation keeps your face looking perfectly just like the start of the day and prevents further darkening of skin. The lightweight, low-viscosity formula helps the foundation adhere to skin instantly while providing excellent coverage just like a liquid foundation.

Directions: Take a small amount with the Ruby Cell Puff and spread evenly over face Please make sure to close the lid after use.